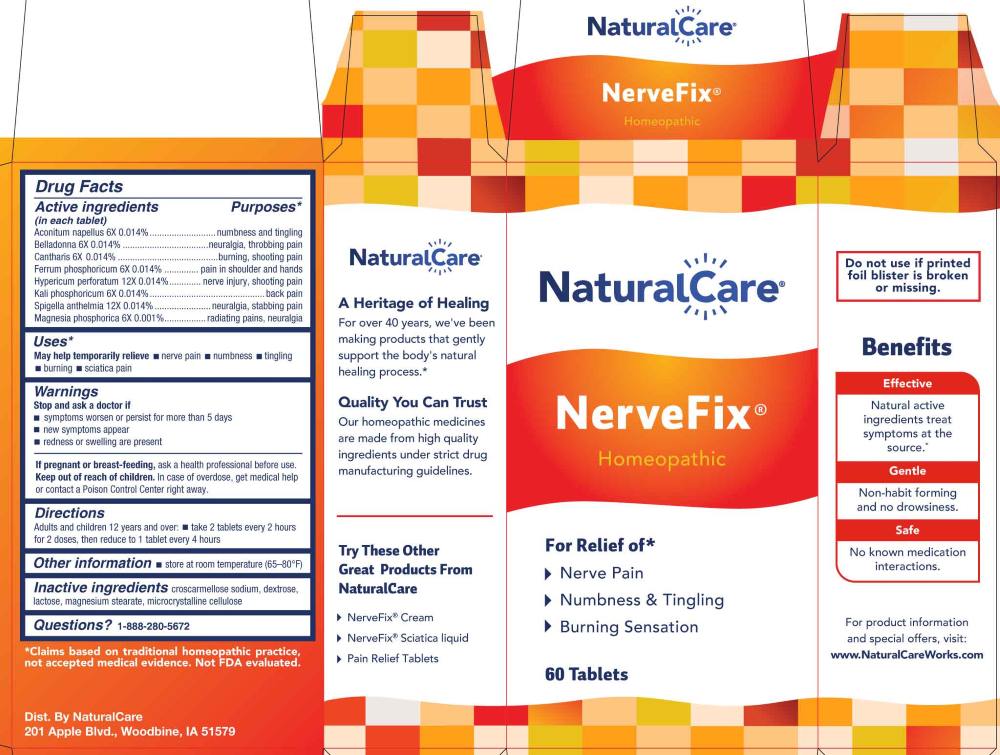 DRUG LABEL: NerveFix
NDC: 70163-0004 | Form: TABLET
Manufacturer: NaturalCare
Category: homeopathic | Type: HUMAN OTC DRUG LABEL
Date: 20260203

ACTIVE INGREDIENTS: ACONITUM NAPELLUS WHOLE 6 [hp_X]/1 1; ATROPA BELLADONNA 6 [hp_X]/1 1; LYTTA VESICATORIA 6 [hp_X]/1 1; FERROSOFERRIC PHOSPHATE 6 [hp_X]/1 1; DIBASIC POTASSIUM PHOSPHATE 6 [hp_X]/1 1; MAGNESIUM PHOSPHATE, DIBASIC TRIHYDRATE 6 [hp_X]/1 1; HYPERICUM PERFORATUM WHOLE 12 [hp_X]/1 1; SPIGELIA ANTHELMIA WHOLE 12 [hp_X]/1 1
INACTIVE INGREDIENTS: CROSCARMELLOSE SODIUM; DEXTROSE, UNSPECIFIED FORM; LACTOSE MONOHYDRATE; MAGNESIUM STEARATE; MICROCRYSTALLINE CELLULOSE

DRUG FACTS:

ACTIVE INGREDIENT:

(in each tablet) Aconitum Napellus 6X 0.014%, Belladonna 6X 0.014%, Cantharis 6X 0.014%, Ferrum Phosphoricum 6X 0.014%, Hypericum Perforatum 12X 0.014%, Kali Phosphoricum 6X 0.014%, Spigelia Anthelmia 12X 0.014%, Magnesia Phosphorica 6X 0.001%

PURPOSE:

Aconitum Napellus – numbness and tingling, Belladonna – neuralgia, throbbing pain, Cantharis – burning, shooting pain, Ferrum Phosphoricum – pain in shoulder and hands, Hypericum Perforatum – nerve injury, shooting pain, Kali Phosphoricum – back pain, Spigelia Anthelmia – neuralgia, stabbing pain, Magnesia Phosphorica – radiating pains, neuralgia*

*Claims based on traditional homeopathic practice, not accepted medical evidence. Not FDA evaluated.

USES:

May help temporarily relieve ■ nerve pain ■ numbness ■ tingling ■ burning ■ sciatica pain*

*Claims based on traditional homeopathic practice, not accepted medical evidence. Not FDA evaluated.

WARNINGS:

Stop use and ask a doctor if

■ symptoms worsen or persist for more than 5 days

■ new symptoms appear

■ redness or swelling are present

If pregnant or breast-feeding, ask a health professional before use.

Keep out of reach of children. In case of overdose, get medical help or contact a Poison Control Center right away.

Do not use if printed foil blister is broken or missing.

■ Store at room temperature (65-80ºF)

KEEP OUT OF REACH OF CHILDREN:

In case of overdose, get medical help or contact a Poison Control Center right away.

DIRECTIONS:

Adults and children 12 years and over:

■ take 2 tablets every 2 hours for 2 doses, then reduce to 1 tablet every 4 hours.

INACTIVE INGREDIENTS:

croscarmellose sodium, dextrose, lactose, magnesium stearate, microcrystalline cellulose

QUESTIONS:

Dist. By NaturalCare

201 Apple Blvd.

Woodbine, IA 51579

www.NaturalCareWorks.com

1-888-280-5672

PACKAGE LABEL DISPLAY:

NaturalCare

NerveFix

Homeopathic

For Relief of*

Nerve Pain

Numbness & Tingling

Burning Sensation

60 Tablets